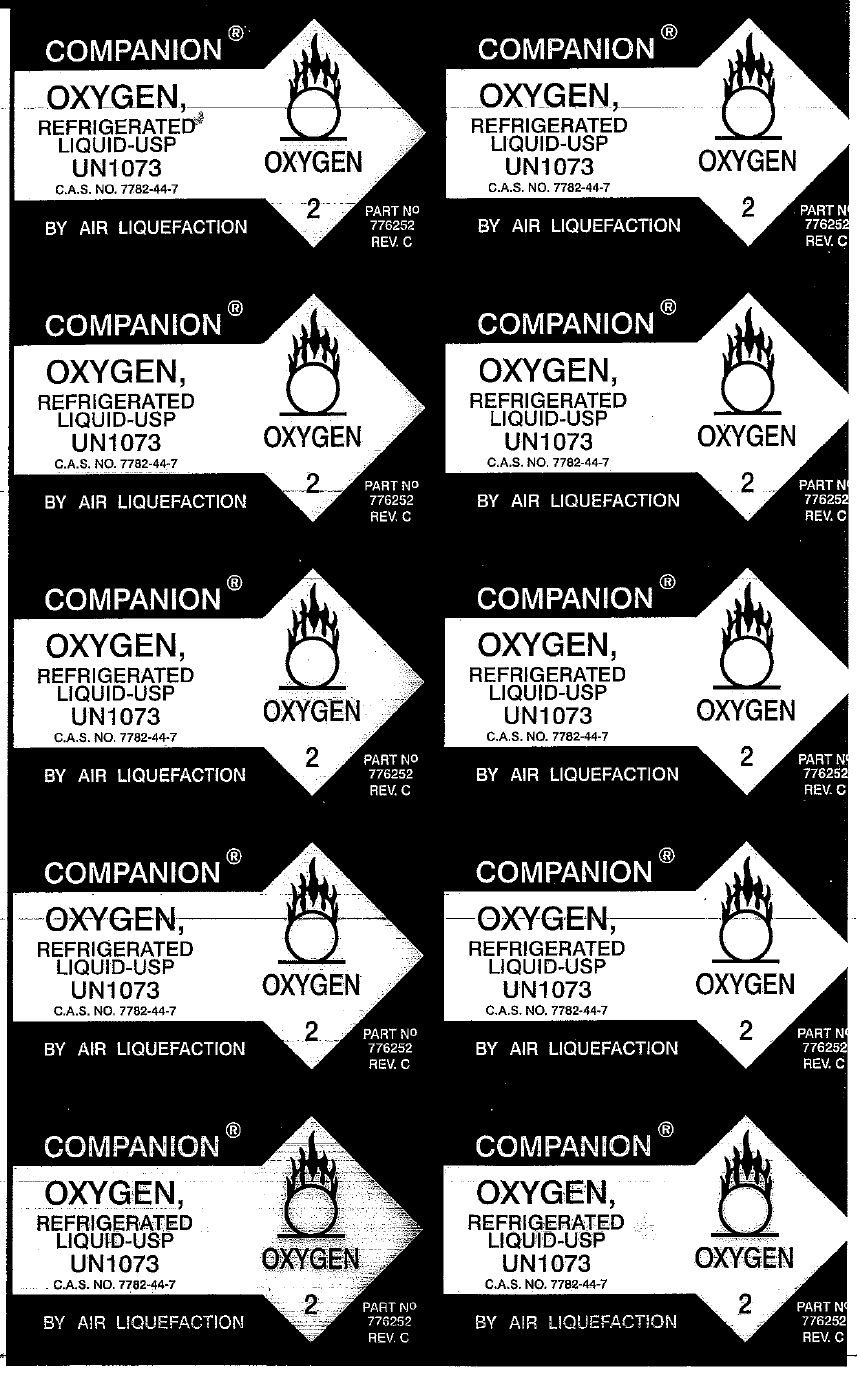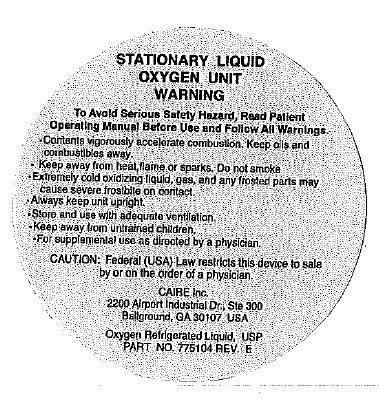 DRUG LABEL: Oxygen Refrigerated Liquid
NDC: 61888-0202 | Form: GAS
Manufacturer: Elliot Hospital of the City of Manchester DBA: Home Medical Equipment and Infusion Services of Manchester & Southern N.H.
Category: prescription | Type: HUMAN PRESCRIPTION DRUG LABEL
Date: 20221004

ACTIVE INGREDIENTS: OXYGEN 0.99 kg/1 kg

Oxygen Refrigerated Liquid-USP